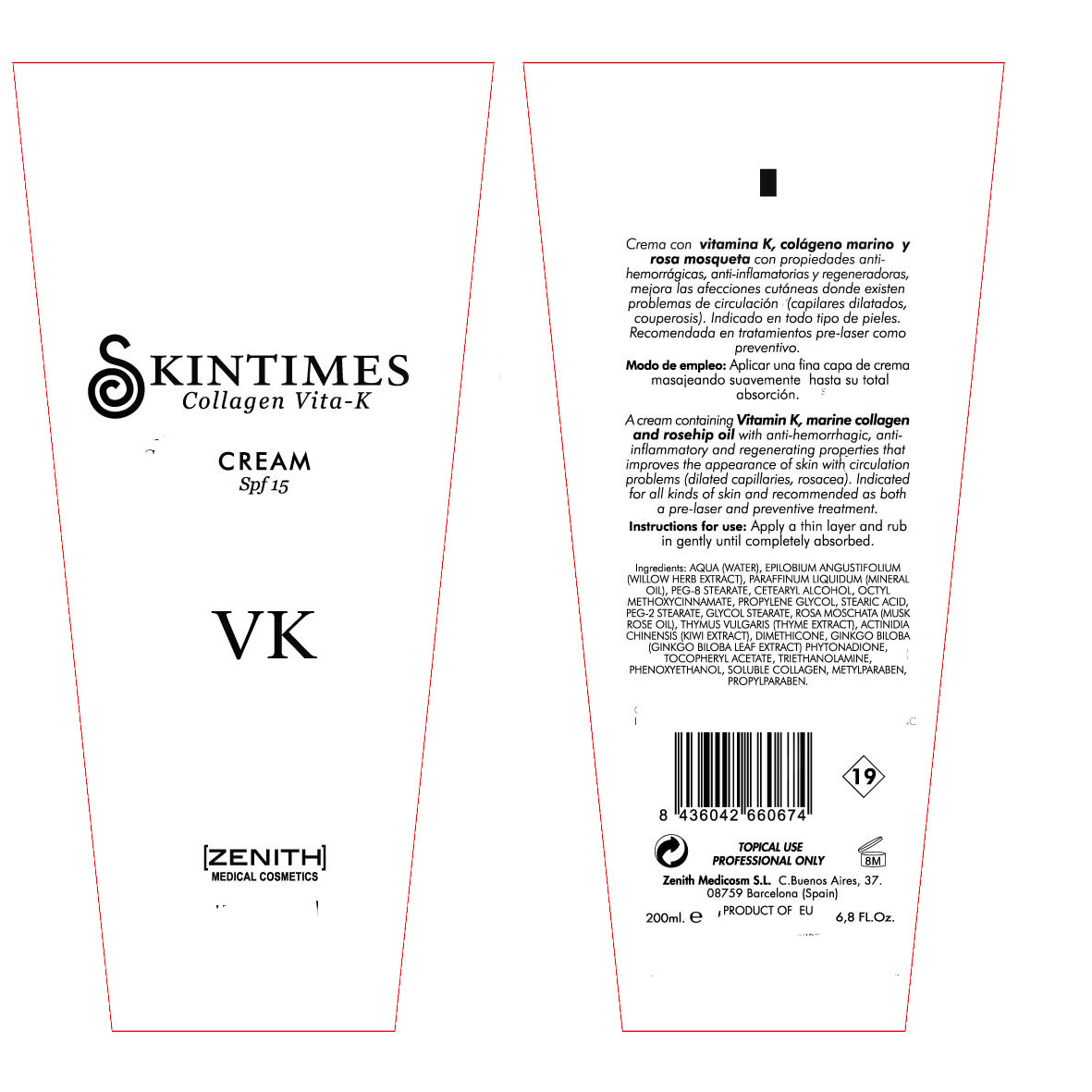 DRUG LABEL: Vita
NDC: 42248-118 | Form: CREAM
Manufacturer: Zenith Medicosm SL
Category: otc | Type: HUMAN OTC DRUG LABEL
Date: 20120121

ACTIVE INGREDIENTS: OCTINOXATE 15 mL/200 mL
INACTIVE INGREDIENTS: PEG-2 STEARATE; PROPYLPARABEN; ALPHA-TOCOPHEROL ACETATE; DIMETHICONE; GLYCOL STEARATE; ROSA MOSCHATA OIL; WATER; MINERAL OIL; CETOSTEARYL ALCOHOL; PEG-8 STEARATE; TROLAMINE; THYME; KIWI FRUIT; PHYTONADIONE; METHYLPARABEN; COLLAGEN, SOLUBLE, FISH SKIN; STEARIC ACID; PROPYLENE GLYCOL; EPILOBIUM ANGUSTIFOLIUM LEAF; GINKGO; PHENOXYETHANOL

Drug Facts

Active Ingredient

Octinoxate 7.5%

Description

A cream containing Vitamin K, marine collagen, rosehip oil with anti-hemorrhagic,anti-inflammatory and regenerating properties that improves the appearance of skin with circulation problems (dilated capillaries, rosacea). Indicated for all kinds of skin and recommended as both a pre-laser and preventive treatment.

200ml. 6.8Fl.Oz.

Warning

TOPICAL USE

PROFESSIONAL ONLY

Instructions For Use:

Apply a thin layer and rub in gently until completely absorbed.